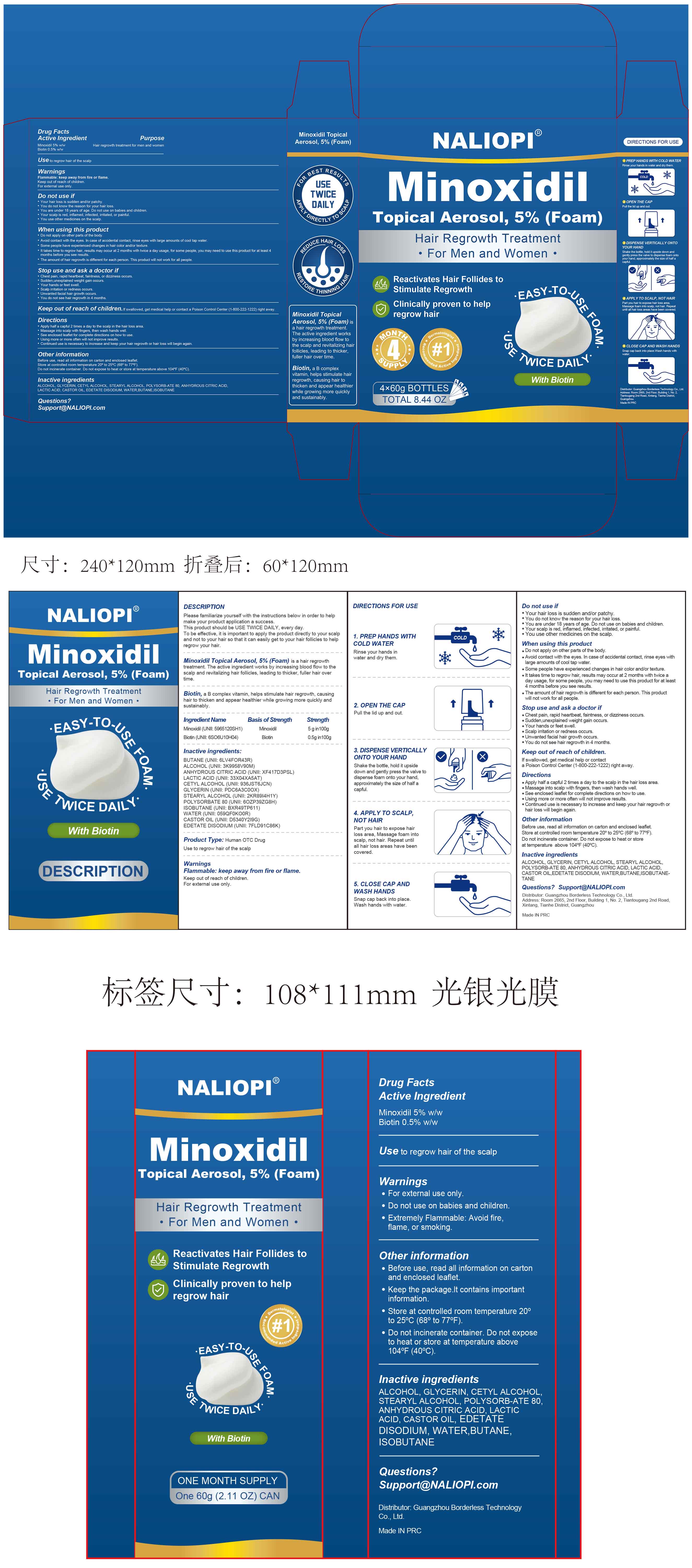 DRUG LABEL: 5% Minoxidil Hair Growth Foam
NDC: 85304-019 | Form: AEROSOL, FOAM
Manufacturer: Guangzhou Borderless Technology Co., Ltd.
Category: otc | Type: HUMAN OTC DRUG LABEL
Date: 20250929

ACTIVE INGREDIENTS: MINOXIDIL 5 g/100 g; BIOTIN 0.5 g/100 g
INACTIVE INGREDIENTS: LACTIC ACID; EDETATE DISODIUM; ALCOHOL; CETYL ALCOHOL; POLYSORBATE 60; WATER; BUTANE; STEARYL ALCOHOL; ISOBUTANE; CITRIC ACID; GLYCERIN

85304-019 5% Minoxidil Hair Growth Foam

ACTIVE INGREDIENT

Minoxidil 5%
Biotin 0.5%

PURPOSE

Hair regrowth treatment for men and women

INDICATIONS AND USAGE

Use to regrow hair of the scalp

WARNINGS

Flammable: keep away from fire or flame.
Keep out of reach of children.
For extemal use only.

DO NOT USE

Your hair loss is sudden and/or patchy.
You do not know the reason for your hair loss.
You are under 18 years of age, Do not use on babies and children.
Your scalp is red, inflamed, infected, irritated or painful.
You use other medicines on the scalp.

WHEN USING

Do not apply on other parts of the body.
Avoid contact with the eyes. in case of accidental contact, rinse eyes with large amounts of cool tap water.
Some people have experienced changes in hair color and/or texture.
It takes ime to regrow hair, results may occur at2 months with twice a day usage, for some people, you may need to use this product for at least 4 months before you see results.
The amount of hair regrowth is diferent for each person. This product wil not work for all people.

STOP USE

Chest pain,rapid heartbeat faintness, or dizziness occurs.
Sudden,unexplained weight gain oceurs.
Your hands or feet swell.
Scalp irritation or redness occurs.
Unwanted facial hair growth occurs.
You do not see hair regrowth in 4 months.

Keep out of reach of children. if swalowed, get medical help or contact a Poison control Center (1-800-222-1222) right away.

DOSAGE AND ADMINISTRATION

Apply half a capful 2 times a day to the scalp in the hair loss area.
Massage into scalp with fingers, then wash hands well..
See enclosed leaflet for complete directions on how to use.
Using more or more often will not improve results.
Continued use is necessary to increase and keep your hair regrowth or hair loss will begin again.

INACTIVE INGREDIENT

cetyl alcohol
citric acid
glycerin
isobutane
lactic acid
polysorbate 60
purified water
SD alcohol 40-B
stearyl alcohol
butane
edetate disodium